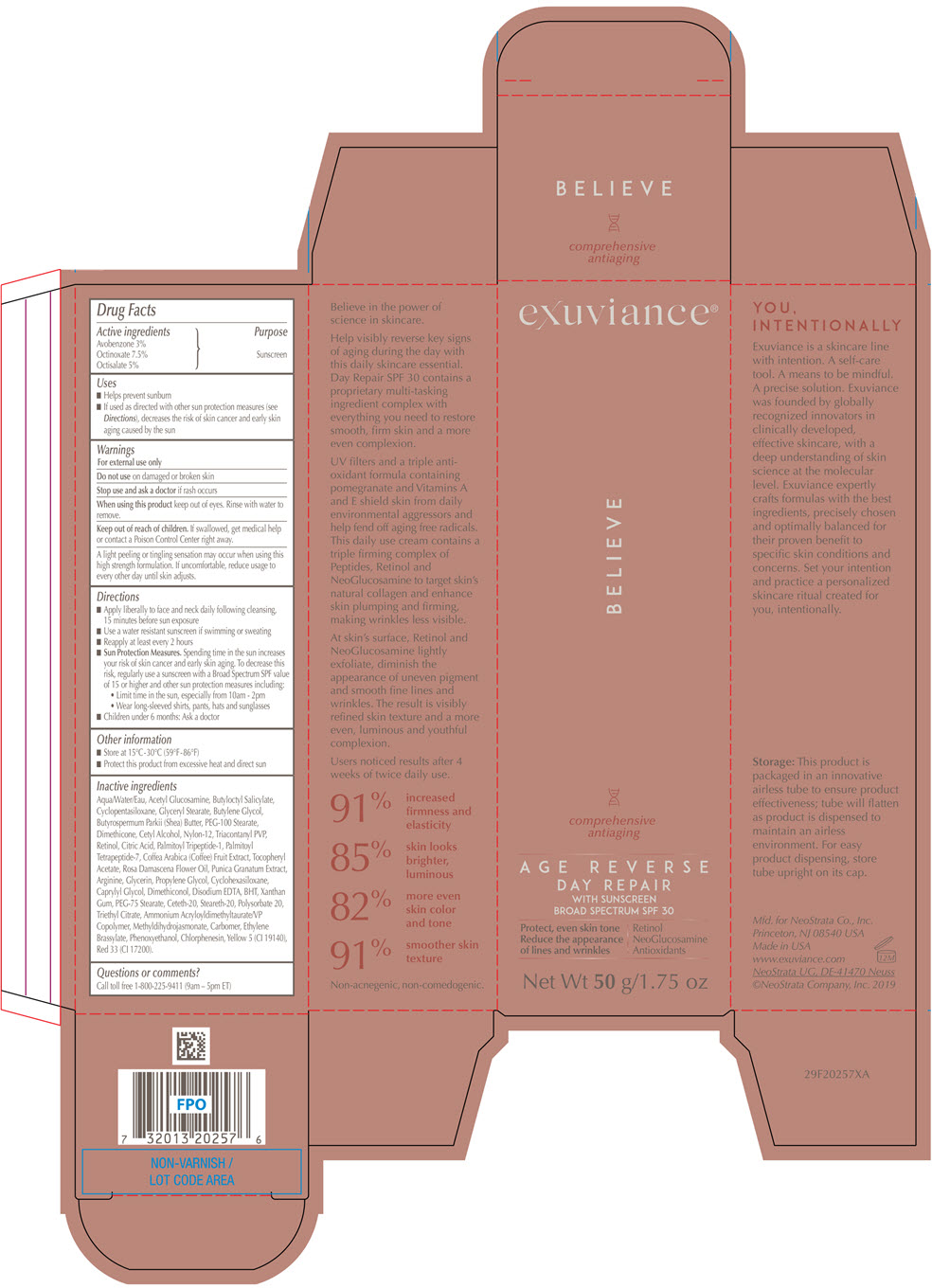 DRUG LABEL: Exuviance Age Reverse Day Repair
NDC: 58414-0023 | Form: CREAM
Manufacturer: NeoStrata Company Inc.
Category: otc | Type: HUMAN OTC DRUG LABEL
Date: 20260301

ACTIVE INGREDIENTS: AVOBENZONE 30 mg/1 g; OCTINOXATE 75 mg/1 g; OCTISALATE 50 mg/1 g
INACTIVE INGREDIENTS: WATER; N-ACETYLGLUCOSAMINE; BUTYLOCTYL SALICYLATE; CYCLOMETHICONE 5; GLYCERYL MONOSTEARATE; BUTYLENE GLYCOL; SHEA BUTTER; PEG-100 STEARATE; DIMETHICONE; CETYL ALCOHOL; NYLON-12; TRICONTANYL POVIDONE; RETINOL; .ALPHA.-TOCOPHEROL ACETATE; PALMITOYL TRIPEPTIDE-1; PALMITOYL TETRAPEPTIDE-7; PUNICA GRANATUM ROOT BARK; COFFEA ARABICA FRUIT; ROSA X DAMASCENA FLOWER OIL; ARGININE; GLYCERIN; PROPYLENE GLYCOL; TRIETHYL CITRATE; CYCLOMETHICONE 6; CAPRYLYL GLYCOL; CITRIC ACID MONOHYDRATE; EDETATE DISODIUM ANHYDROUS; BUTYLATED HYDROXYTOLUENE; PEG-75 STEARATE; CETETH-20; STEARETH-20; DIMETHICONOL (100000 CST); POLYSORBATE 20; XANTHAN GUM; AMMONIUM ACRYLOYLDIMETHYLTAURATE/VP COPOLYMER; METHYL DIHYDROJASMONATE (SYNTHETIC); CARBOMER HOMOPOLYMER, UNSPECIFIED TYPE; ETHYLENE BRASSYLATE; CHLORPHENESIN; PHENOXYETHANOL; FD&C YELLOW NO. 5; D&C RED NO. 33

Exuviance®Age Reverse Day Repair
with Sunscreen Broad Spectrum SPF 30

Drug Facts

Active ingredients

Avobenzone 3%
Octinoxate 7.5%
Octisalate 5%

Purpose

Sunscreen

Uses

- Helps prevent sunburn
- If used as directed with other sun protection measures (see Directions), decreases the risk of skin cancer and early skin aging caused by the sun

Warnings

For external use only

Do not useon damaged or broken skin

Stop use and ask a doctorif rash occurs

WHEN USING

When using this productkeep out of eyes. Rinse with water to remove.

Keep out of reach of children. If swallowed, get medical help or contact a Poison Control Center right away.

A light peeling or tingling sensation may occur when using this high strength formulation. If uncomfortable, reduce usage to every other day until skin adjusts.

Directions

- Apply liberally to face and neck daily following cleansing, 15 minutes before sun exposure
- Use a water resistant sunscreen if swimming or sweating
- Reapply at least every 2 hours
- Sun Protection Measures.Spending time in the sun increases your risk of skin cancer and early skin aging. To decrease this risk, regularly use a sunscreen with a Broad Spectrum SPF value of 15 or higher and other sun protection measures including:
  - Limit time in the sun, especially from 10 am – 2 pm
  - Wear long-sleeved shirts, pants, hats and sunglasses
- Children under 6 months: Ask a doctor

Other information

- Store at 15°C-30°C (59°F – 86°F)
- Protect this product from excessive heat and direct sun

Inactive ingredients

Water, Acetyl Glucosamine, Butyloctyl Salicylate, Cyclopentasiloxane, Glyceryl Stearate, Butylene Glycol, Butyrospermum Parkii (Shea) Butter, PEG-100 Stearate, Dimethicone, Cetyl Alcohol, Nylon-12, Triacontanyl PVP, Retinol, Citric Acid, Palmitoyl Tripeptide-1, Palmitoyl Tetrapeptide-7, Coffea Arabica (Coffee) Fruit Extract, Tocopheryl Acetate, Rosa Damascena Flower Oil, Punica Granatum Extract, Arginine, Glycerin, Propylene Glycol, Cyclohexasiloxane, Caprylyl Glycol, Dimethiconol, Disodium EDTA, BHT, Xanthan Gum, PEG-75 Stearate, Ceteth-20, Steareth-20, Polysorbate 20, Triethyl Citrate, Ammonium Acryloyldimethyltaurate/VP Copolymer, Methyldihydrojasmonate, Carbomer, Ethylene Brassylate, Phenoxyethanol, Chlorphenesin, Yellow 5 (CI 19140), Red 33 (CI 17200).

Questions or comments?

Call toll-free 1-800-225-9411 (9am – 5pm ET)

PRINCIPAL DISPLAY PANEL - 50 g Tube Carton

exuviance®

BELIEVE

comprehensive
antiaging

AGE REVERSE
DAY REPAIR
WITH SUNSCREEN
BROAD SPECTRUM SPF 30
Protect, even skin tone
Reduce the appearance
of lines and wrinkles
Retinol
NeoGlucosamine
Antioxidants
Net Wt 50 g/1.75 oz